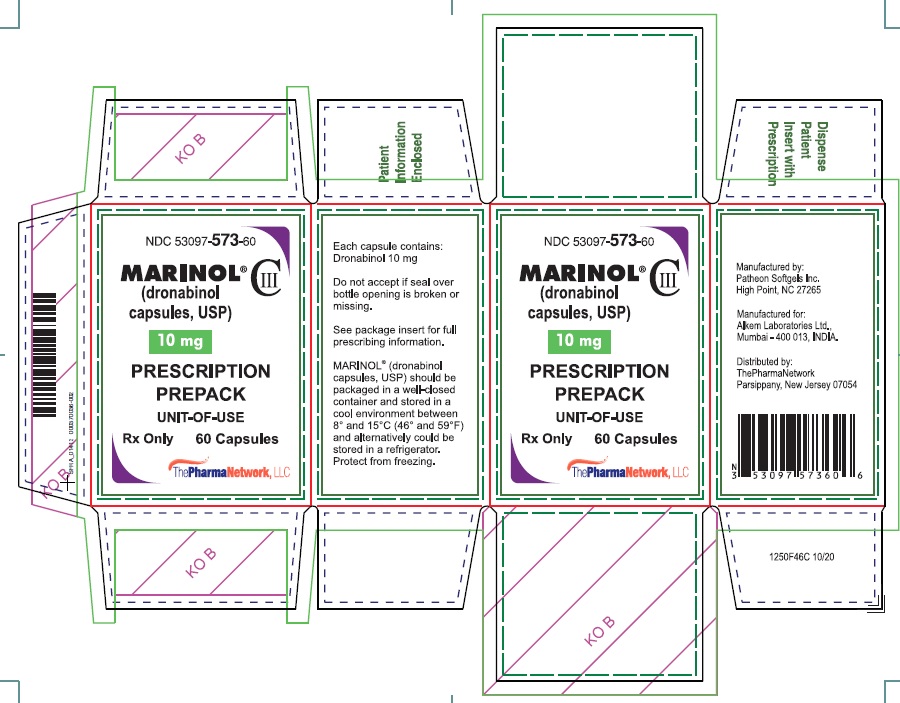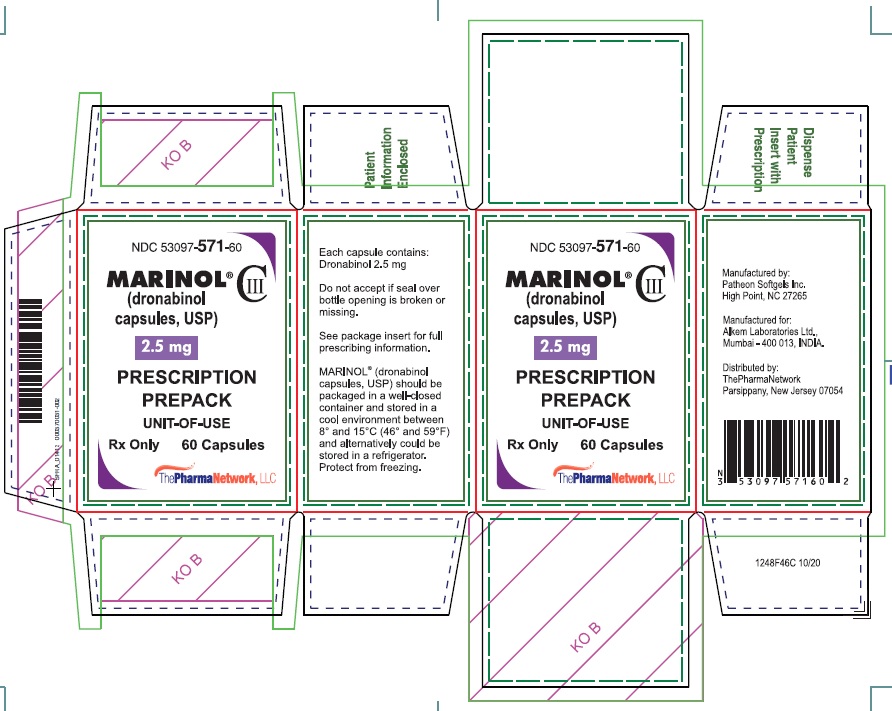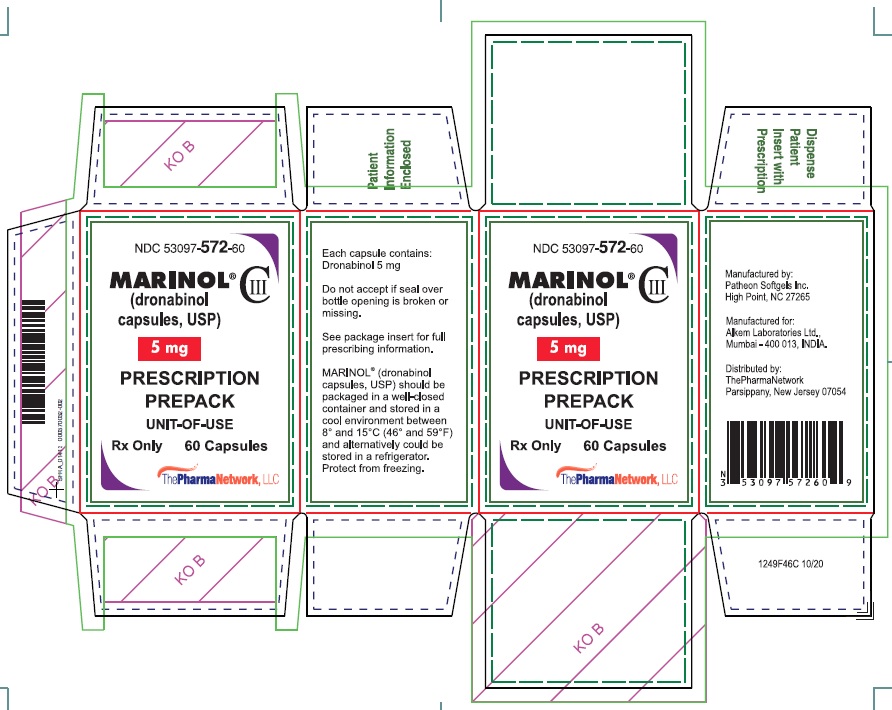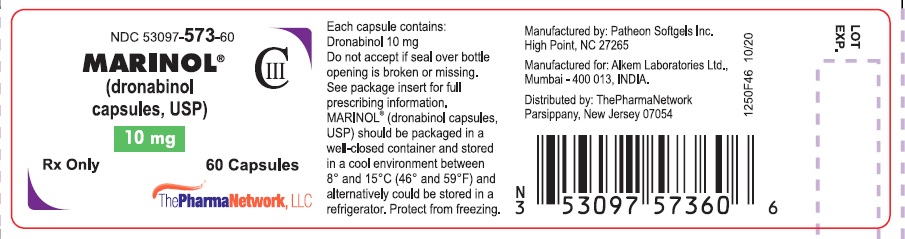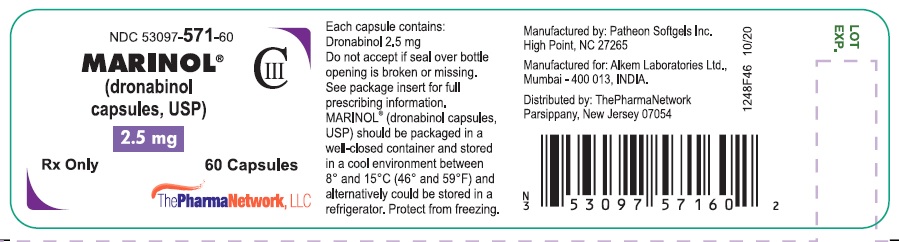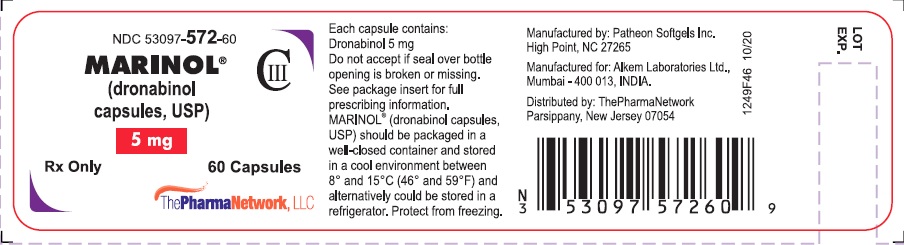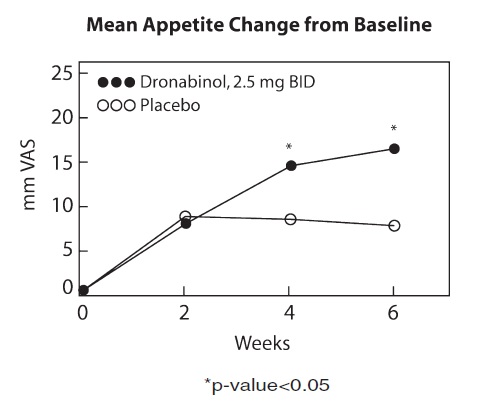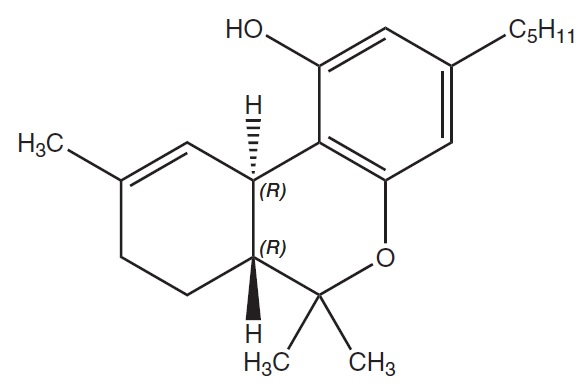 DRUG LABEL: MARINOL
NDC: 53097-571 | Form: CAPSULE
Manufacturer: ThePharmaNetwork, LLC
Category: prescription | Type: Human Prescription Drug Label
Date: 20230214
DEA Schedule: CIII

ACTIVE INGREDIENTS: DRONABINOL 2.5 mg/1 1
INACTIVE INGREDIENTS: GELATIN, UNSPECIFIED; GLYCERIN; SESAME OIL; TITANIUM DIOXIDE

HIGHLIGHTS OF PRESCRIBING INFORMATION

These highlights do not include all the information needed to use MARINOL® safely and effectively. See full prescribing information for MARINOL.
MARINOL (dronabinol) capsules, for oral use, CIII
Initial U.S. Approval: 1985

1 INDICATIONS AND USAGE

MARINOL is a cannabinoid indicated in adults for the treatment of:

- Anorexia associated with weight loss in patients with AIDS. (1)
- Nausea and vomiting associated with cancer chemotherapy in patients who have failed to respond adequately to conventional antiemetic treatments. (1)

2 DOSAGE AND ADMINISTRATION

Anorexia Associated with Weight Loss in Adult Patients with AIDS (2.1):

- The recommended adult starting dosage is 2.5 mg orally twice daily, one hour before lunch and dinner.
- See the full prescribing information for dosage titration to manage adverse reactions and to achieve desired therapeutic effect.

Nausea and Vomiting Associated with Chemotherapy in Adult Patients Who Failed Conventional Antiemetics (2.2):

- The recommended starting dosage is 5 mg/m^2, administered 1 to 3 hours prior to the administration of chemotherapy, then every 2 to 4 hours after chemotherapy, for a total of 4 to 6 doses per day. Administer the first dose on an empty stomach at least 30 minutes prior to eating; subsequent doses can be taken without regard to meals.
- See the full prescribing information for dosage titration to manage adverse reactions and to achieve desired therapeutic effect.

3 DOSAGE FORMS AND STRENGTHS

- Capsules: 2.5 mg, 5 mg, 10 mg (3)

4 CONTRAINDICATIONS

- History of a hypersensitivity reaction to dronabinol or sesame oil (4)

5 WARNINGS AND PRECAUTIONS

- Neuropsychiatric Adverse Reactions: May cause psychiatric and cognitive effects and impair mental and/or physical abilities. Avoid use in patients with a psychiatric history. Monitor for symptoms and avoid concomitant use of drugs with similar effects. Inform patients not to operate motor vehicles or other dangerous machinery until they are reasonably certain that MARINOL® (dronabinol capsules, USP), does not affect them adversely. (5.1)
- Hemodynamic Instability: Patients with cardiac disorders may experience hypotension, hypertension, syncope or tachycardia. Avoid concomitant use of drugs with similar effects and monitor for hemodynamic changes after initiating or increasing the dosage of MARINOL. (5.2)
- Seizures and Seizure-like Activity: Weigh the potential risk versus benefits before prescribing MARINOL to patients with a history of seizures, including those requiring anti-epileptic medication or with other factors that lower the seizure threshold. Monitor patients and discontinue if seizures occur. (5.3)
- Multiple Substance Abuse: Assess risk for abuse or misuse in patients with a history of substance abuse or dependence, prior to prescribing MARINOL and monitor for the development of associated behaviors or conditions. (5.4)
- Paradoxical Nausea, Vomiting, or Abdominal Pain: Consider dose reduction or discontinuation, if worsening of symptoms while on treatment. (5.5)

6 ADVERSE REACTIONS

- Most common adverse reactions (≥3%) are: abdominal pain, dizziness, euphoria, nausea, paranoid reaction, somnolence, thinking abnormal and vomiting. (6.1)

To report SUSPECTED ADVERSE REACTIONS, contact The Pharma Network, LLC at 1-877-272-7901 or FDA at 1-800-FDA-1088 or www.fda.gov/medwatch.

7 DRUG INTERACTIONS

- Inhibitors and inducers of CYP2C9 and CYP3A4: May alter dronabinol systemic exposure; monitor for potential dronabinol-related adverse reactions or loss of efficacy. (7.3)
- Highly protein-bound drugs: Potential for displacement of other drugs from plasma proteins; monitor for adverse reactions to concomitant highly protein-bound drugs and narrow therapeutic index drugs (e.g., warfarin, cyclosporine, amphotericin B) when initiating or increasing the dosage of MARINOL. (7.4)

8 USE IN SPECIFIC POPULATIONS

- Pregnancy: May cause fetal harm. (8.1)
- Lactation: Advise HIV-infected women not to breastfeed due to the potential for HIV transmission. Weight should be monitored in breastfed infants of mothers with nausea and vomiting associated with cancer chemotherapy in whom breastfeeding is appropriate. (8.2)
- Geriatric Use: Elderly patients may be more sensitive to the neuropsychiatric and postural hypotensive effects. Consider a lower starting dose in elderly patients. (2.1,2.2, 5.1, 5.2, 8.5)

FULL PRESCRIBING INFORMATION

1 INDICATIONS AND USAGE

MARINOL is indicated in adults for the treatment of:

- anorexia associated with weight loss in patients with Acquired Immune Deficiency Syndrome (AIDS).
- nausea and vomiting associated with cancer chemotherapy in patients who have failed to respond adequately to conventional antiemetic treatments.

2 DOSAGE AND ADMINISTRATION

2.1 Anorexia Associated with Weight Loss in Adult Patients with AIDS

Starting Dosage
The recommended adult starting dosage of MARINOL is 2.5 mg orally twice daily, one hour before lunch and dinner.
In elderly patients or patients unable to tolerate 2.5 mg twice daily, consider initiating MARINOL at 2.5 mg once daily one hour before dinner or at bedtime to reduce the risk of central nervous system (CNS) symptoms [see Use in Specific Populations (8.5)].
Dosing later in the day may reduce the frequency of CNS adverse reactions. CNS adverse reactions are dose-related [see Warnings and Precautions (5.1)]; therefore monitor patients and reduce the dosage as needed. If CNS adverse reactions of feeling high, dizziness, confusion, and somnolence occur, they usually resolve in 1 to 3 days and usually do not require dosage reduction. If CNS adverse reactions are severe or persistent, reduce the dosage to 2.5 mg in the evening or at bedtime.
Dosage Titration
If tolerated and further therapeutic effect is desired, the dosage may be increased gradually to 2.5 mg one hour before lunch and 5 mg one hour before dinner. Increase the dose of MARINOL gradually in order to reduce the frequency of dose-related adverse reactions [see Warnings and Precautions (5.1)].
Most patients respond to 2.5 mg twice daily, but the dose may be further increased to 5 mg one hour before lunch and 5 mg one hour before dinner, as tolerated to achieve a therapeutic effect.
Maximum Dosage: 10 mg twice daily.

2.2 Nausea and Vomiting Associated with Cancer Chemotherapy in Adult Patients Who Failed Conventional Antiemetics

Starting Dosage

The recommended starting dosage of MARINOL is 5 mg/m^2, orally administered 1 to 3 hours prior to the administration of chemotherapy and then every 2 to 4 hours after chemotherapy, for a total of 4 to 6 doses per day.

In elderly patients, consider initiating MARINOL at 2.5 mg/m^2 once daily 1 to 3 hours prior to chemotherapy to reduce the risk of CNS symptoms [see Use in Specific Populations (8.5)].

Administer the first dose on an empty stomach at least 30 minutes before eating. Subsequent doses can be taken without regard to meals [see Clinical Pharmacology (12.3)].

The timing of dosing in relation to meal times should be kept consistent for each chemotherapy cycle, once the dosage has been determined from the titration process.

Dosage Titration

The dosage can be titrated to clinical response during a chemotherapy cycle or subsequent cycles, based upon initial response, as tolerated to achieve a clinical effect, in increments of 2.5 mg/m^2.

The maximum dosage is 15 mg/m^2 per dose for 4 to 6 doses per day.

Adverse reactions are dose-related and psychiatric symptoms increase significantly at the maximum dosage [see Warnings and Precautions (5.1)]. Monitor patients for adverse reactions and consider decreasing the dose to 2.5 mg once daily 1 to 3 hours prior to chemotherapy to reduce the risk of CNS adverse reactions.

3 DOSAGE FORMS AND STRENGTHS

MARINOL is supplied as round, soft gelatin capsules for oral use as follows:

- 2.5 mg white capsules (Identified M2)
- 5 mg dark brown capsules (Identified M5)
- 10 mg orange capsules (Identified MX)

4 CONTRAINDICATIONS

MARINOL® (dronabinol capsules, USP), is contraindicated in patients with a history of a hypersensitivity reaction to dronabinol or sesame oil. Reported hypersensitivity reactions to dronabinol capsules include lip swelling, hives, disseminated rash, oral lesions, skin burning, flushing and throat tightness [see Adverse Reactions (6.2)].

5 WARNINGS AND PRECAUTIONS

5.1 Neuropsychiatric Adverse Reactions

Psychiatric Adverse Reactions

Dronabinol has been reported to exacerbate mania, depression, or schizophrenia. Significant CNS symptoms followed oral doses of 0.4 mg/kg (28 mg per 70 kg patient) of MARINOL in antiemetic studies.

Prior to initiating treatment with MARINOL, screen patients for a history of these illnesses. Avoid use in patients with a psychiatric history or, if the drug cannot be avoided, monitor patients for new or worsening psychiatric symptoms during treatment. Also, avoid concomitant use with other drugs that are associated with similar psychiatric effects.

Cognitive Adverse Reactions

Use of MARINOL has been associated with cognitive impairment and altered mental state. Reduce the dose of MARINOL or discontinue use of MARINOL if signs or symptoms of cognitive impairment develop. Elderly patients may be more sensitive to the neurological and psychoactive effects of MARINOL [see Use in Specific Populations (8.4, 8.5)].

Hazardous Activities

MARINOL can cause and may impair the mental and/or physical abilities required for the performance of hazardous tasks such as driving a motor vehicle or operating machinery. Concomitant use of other drugs that cause dizziness, confusion, sedation, or somnolence such as CNS depressants may increase this effect (e.g., barbiturates, benzodiazepines, ethanol, lithium, opioids, buspirone, scopolamine, antihistamines, tricyclic antidepressants, other anticholinergic agents, muscle relaxants). Inform patients not to operate motor vehicles or other dangerous machinery until they are reasonably certain that MARINOL does not affect them adversely.

5.2 Hemodynamic Instability

Patients may experience occasional hypotension, possible hypertension, syncope, or tachycardia while taking MARINOL [see Clinical Pharmacology (12.2)]. Patients with cardiac disorders may be at higher risk. Avoid concomitant use of other drugs that are also associated with similar cardiac effects (e.g., amphetamines, other sympathomimetic agents, atropine, amoxapine, scopolamine, antihistamines, other anticholinergic agents, amitriptyline, desipramine, other tricyclic antidepressants). Monitor patients for changes in blood pressure, heart rate, and syncope after initiating or increasing the dosage of MARINOL.

5.3 Seizures

Seizure and seizure-like activity have been reported in patients receiving dronabinol. Weigh this potential risk against the benefits before prescribing MARINOL to patients with a history of seizures, including those receiving anti-epileptic medication or with other factors that can lower the seizure threshold. Monitor patients with a history of seizure disorders for worsened seizure control during MARINOL therapy.

If a seizure occurs, advise patients to discontinue MARINOL and contact a healthcare provider immediately.

5.4 Multiple Substance Abuse

Patients with a history of substance abuse or dependence, including marijuana or alcohol, may be more likely to abuse MARINOL as well.

Assess each patient’s risk for abuse or misuse prior to prescribing MARINOL and monitor patients with a history of substance abuse during treatment with MARINOL for the development of these behaviors or conditions.

5.5 Paradoxical Nausea, Vomiting, or Abdominal Pain

Nausea, vomiting, or abdominal pain can occur during treatment with synthetic delta-9- tetrahydrocannabinol (delta-9-THC), the active ingredient in MARINOL® (dronabinol capsules, USP). In some cases, these adverse reactions were severe (e.g., dehydration, electrolyte abnormalities) and required dose reduction or drug discontinuation. Symptoms are similar to cannabinoid hyperemesis syndrome (CHS), which is described as cyclical events of abdominal pain, nausea, and vomiting in chronic, long-term users of delta-9-THC products.

Because patients may not recognize these symptoms as abnormal, it is important to specifically ask patients or their caregivers about the development of worsening of nausea, vomiting, or abdominal pain while being treated with MARINOL. Consider dose reduction or discontinuing MARINOL if a patient develops worsening nausea, vomiting, or abdominal pain while on treatment.

6 ADVERSE REACTIONS

6.1 Clinical Trials Experience

Because clinical trials are conducted under widely varying conditions, adverse reaction rates observed in the clinical trials of a drug cannot be directly compared to rates in the clinical trials of another drug and may not reflect the rates observed in practice.

The following serious adverse reactions are described below and elsewhere in the labeling.

- Neuropsychiatric Adverse Reactions [see Warnings and Precautions (5.1)]
- Hemodynamic Instability [see Warnings and Precautions (5.2)]
- Seizures [see Warnings and Precautions (5.3)]
- Paradoxical Nausea, Vomiting, and Abdominal Pain [see Warnings and Precautions (5.5)]

Studies of AIDS-related weight loss included 157 patients receiving MARINOL at a dose of 2.5 mg twice daily and 67 receiving placebo. Studies of nausea and vomiting related to cancer chemotherapy included 317 patients receiving MARINOL and 68 receiving placebo. In the tables below is a summary of the adverse reactions in 474 patients exposed to MARINOL in studies. Studies of different durations were combined by considering the first occurrence of events during the first 28 days.

A cannabinoid dose-related “high” (easy laughing, elation and heightened awareness) has been reported by patients receiving MARINOL in both the antiemetic (24%) and the lower dose appetite stimulant clinical trials (8%). The most frequently reported adverse experiences in patients with AIDS during placebo-controlled clinical trials involved the CNS and were reported by 33% of patients receiving MARINOL. About 25% of patients reported a CNS adverse reaction during the first 2 weeks and about 4% reported such a reaction each week for the next 6 weeks thereafter.

Common Adverse Reactions

The following adverse reactions were reported in clinical trials at an incidence greater than 1%.

System Organ Class | Adverse Reactions
General | Asthenia
Cardiovascular | Palpitations, tachycardia, vasodilation/facial flush
Gastrointestinal | Abdominal pain*, nausea*, vomiting*
Central Nervous System | Dizziness*, euphoria*, paranoid reaction*, somnolence*, thinking abnormal*, amnesia, anxiety/nervousness, ataxia, confusion, depersonalization, hallucination
* Actual incidence 3% to 10%

Less Common Adverse Reactions
The following adverse reactions were reported in clinical trials at an incidence less than or equal to 1%.

System Organ Class | Adverse Reactions
General | Chills, headache, malaise
Cardiovascular | Hypotension, conjunctival injection [see Clinical Pharmacology (12.2)]
Gastrointestinal | Diarrhea, fecal incontinence, anorexia, hepatic enzyme elevation
Musculoskeletal | Myalgias
Central Nervous System | Depression, nightmares, speech difficulties, tinnitus
Respiratory | Cough, rhinitis, sinusitis
Skin | Flushing, sweating
Sensory | Vision difficulties

6.2 Postmarketing Experience

The following adverse reactions have been identified during post-approval use of dronabinol capsules. Because these reactions are reported voluntarily from a population of uncertain size, it is not always possible to reliably estimate their frequency or establish a causal relationship to drug exposure. General disorders and administration site conditions: Fatigue

Hypersensitivity reactions: Lip swelling, hives, disseminated rash, oral lesions, skin burning, flushing, throat tightness [see Contraindications (4)]

Injury, poisoning and procedural complications: Fall [see Use in Specific Populations (8.5)]

Nervous system disorders: Seizures [see Warnings and Precautions (5.3)], disorientation, movement disorder, loss of consciousness

Psychiatric disorders: Delirium, insomnia, panic attack

Vascular disorders: Syncope [see Warnings and Precautions (5.2)]

7 DRUG INTERACTIONS

7.1 Additive CNS Effects

Additive CNS effects (e.g., dizziness, confusion, sedation, somnolence) may occur when MARINOL is taken concomitantly with drugs that have similar effects on the central nervous system such as CNS depressants [see Warnings and Precautions (5.1)].

7.2 Additive Cardiac Effects

Additive cardiac effects (e.g., hypotension, hypertension, syncope, tachycardia) may occur when MARINOL is taken concomitantly with drugs that have similar effects on the cardiovascular system [see Warnings and Precautions (5.2)].

7.3 Effect of Other Drugs on Dronabinol

Dronabinol is primarily metabolized by CYP2C9 and CYP3A4 enzymes based on published in vitro studies. Inhibitors of these enzymes may increase, while inducers may decrease, the systemic exposure of dronabinol and/or its active metabolite resulting in an increase in dronabinol-related adverse reactions or loss of efficacy of MARINOL.

Monitor for potentially increased dronabinol-related adverse reactions when MARINOL is co-administered with inhibitors of CYP2C9 (e.g., amiodarone, fluconazole) and inhibitors of CYP3A4 enzymes (e.g., ketoconazole, itraconazole, clarithromycin, ritonavir, erythromycin, grapefruit juice).

7.4 Highly Protein-Bound Drugs

Dronabinol is highly bound to plasma proteins, and therefore, might displace and increase the free fraction of other concomitantly administered protein-bound drugs.

Although this displacement has not been confirmed in vivo, monitor patients for increased adverse reactions to narrow therapeutic index drugs that are highly protein-bound (e.g., warfarin, cyclosporine, amphotericin B) when initiating treatment or increasing the dosage of MARINOL.

8 USE IN SPECIFIC POPULATIONS

8.1 Pregnancy

Risk Summary

MARINOL, a synthetic cannabinoid, may cause fetal harm. Avoid use of MARINOL in pregnant women. Although there is little published data on the use of synthetic cannabinoids during pregnancy, use of cannabis (e.g., marijuana) during pregnancy has been associated with adverse fetal/neonatal outcomes (see Clinical Considerations). Cannabinoids have been found in the umbilical cord blood from pregnant women who smoke cannabis. In animal reproduction studies, no teratogenicity was reported in mice administered dronabinol (delta-9-THC) at up to 30 times the MRHD (maximum recommended human dose) and up to 5 times the MRHD for patients with AIDS and cancer, respectively. Similar findings were reported in pregnant rats administered dronabinol at up to 5 to 20 times the MRHD and 3 times the MRHD for patients with AIDS and cancer, respectively. Decreased maternal weight gain and number of viable pups and increased fetal mortality and early resorptions were observed in both species at doses which induced maternal toxicity. In rats, maternal administration of dronabinol from pregnancy (implantation) through weaning was associated with maternal toxicity including adverse clinical signs, increased stillbirths and mortality of offspring, and reduced pup bodyweight at 2 and 6 times the MRHD for patients with AIDS, and less than or equal to the MRHD for patients with cancer. No evidence of neurodevelopmental adverse effects was observed in the offspring at doses up to 6 times the MRHD for patients with AlDS, and up to the MRHD for patients with cancer (see Data).

The estimated background risk of major birth defects and miscarriage for the indicated populations are unknown. All pregnancies have a background risk of birth defect, loss, or other adverse outcomes. In the U.S. general population, the estimated background risk of major birth defects and miscarriage in clinically recognized pregnancies is 2 to 4% and 15 to 20%, respectively.

Clinical Considerations

Fetal/Neonatal Adverse Reactions

Published studies suggest that during pregnancy, the use of cannabis, which includes THC, whether for recreational or medicinal purposes, may increase the risk of adverse fetal/neonatal outcomes including fetal growth restriction, low birth weight, preterm birth, small-for-gestational age, admission to the neonatal intensive care unit, and stillbirth. Therefore, use of cannabis during pregnancy should be avoided.

Data

Human Data

Delta-9-THC has been measured in the cord blood of some infants whose mothers reported prenatal use of cannabis, suggesting that dronabinol may cross the placenta to the fetus during pregnancy. The effects of delta-9-THC on the fetus are not known.

Animal Data

Reproduction studies with dronabinol have been performed in mice at 15 to 450 mg/m2, equivalent to 1 to 30 times the MRHD of 15 mg/m2/day in patients with AIDS or 0.2 to 5 times the MRHD of 90 mg/m2/day in patients with cancer, and in rats at 74 to 295 mg/m2 (equivalent to 5 to 20 times the MRHD of 15 mg/m2/day in patients with AIDS or 0.8 to 3 times the MRHD of 90 mg/m2/day in patients with cancer). These studies have revealed no evidence of teratogenicity due to delta-9-THC. At these dronabinol dosages in mice and rats, delta-9-THC decreased maternal weight gain and number of viable pups and increased fetal mortality and early resorptions. Such effects were dose dependent and less apparent at lower doses that produced less maternal toxicity.

Review of published literature indicates that the endocannabinoid system plays a role in neurodevelopmental processes such as neurogenesis, migration, and synaptogenesis. Exposure of pregnant rats to delta-9-THC (during and after organogenesis) may modulate these processes to result in abnormal patterns of neuronal connectivity and subsequent cognitive impairments in the offspring. Nonclinical toxicity studies in pregnant rats and newborn pups have shown prenatal exposure to delta-9-THC that resulted in impairment of motor function, alteration in synaptic activity, and interference in cortical projection of neuron development in the offspring. Prenatal exposure has shown effects on cognitive function such as learning, short-and long-term memory, attention, decreased ability to remember task, and ability to discriminate between novel and same objects. Overall, prenatal exposure to delta-9-THC has resulted in significant and long-term changes in brain development, cognition, and behavior in rat offspring.

In a pre- and postnatal development study, female rats were administered dronabinol by oral gavage at doses of 0.5, 5, or 15 mg/kg /day (equivalent to 0.2, 2, and 6 times the MRHD for patients with AIDS and 0.03, 0.33, and 1.0 times the MRHD for patients with cancer, respectively, based on body surface area) from gestation day 6 (implantation) through lactation day 20 (weaning). Maternal toxicity including adverse clinical signs (i.e., decreased motor activity, low carriage, abnormal gait, hunched posture, vocalization to touch, ungroomed coat, mild dehydration, piloerection, and splayed hindlimbs), reduced body weight and body weight gain, and decreased food consumption were observed during the gestation period at 2 and 6 times the MRHD for patients with AIDS and 0.33 and 1.0 times the MRHD for patients with cancer, respectively. At the same doses, reduced pup bodyweight, increased stillbirths, and mortality of offspring were observed. No neurodevelopmental adverse effects (i.e., neurobehavioral function, sensory function, motor activity, learning and memory) were observed in pups at maternal doses up 15 mg/kg/day (6 times the MRHD in patients with AIDS or 1.0 times the MRI-ID in patients with cancer).

8.2 Lactation

Risk Summary

For mothers infected with the Human Immunodeficiency Virus (HIV), the Centers for Disease Control and Prevention recommends that HIV-infected mothers not breastfeed their infants to avoid risking postnatal transmission of HIV. Because of the potential for HIV transmission (in HIV-negative infants) and serious adverse reactions in a breastfed infant, instruct mothers not to breastfeed if they are receiving MARINOL® (dronabinol capsules, USP).

For mothers with nausea and vomiting associated with cancer chemotherapy, there are limited data on the presence of dronabinol in human milk, the effects on the breastfed infant, or the effects on milk production. The reported effects of inhaled cannabis transferred to the breastfeeding infant have been inconsistent and insufficient to establish causality. In rat offspring exposed to dronabinol in utero and during lactation, reduced bodyweight was observed during the preweaning (lactation) stage with maternal administration of dronabinol at 2 times and less than the MRHD for patients with AIDS and cancer, respectively.
Breastfeeding infants should have their weight monitored. The developmental and health benefits of breastfeeding should be considered along with the mother's clinical need for MARlNOL and any potential adverse effects on the breastfed infant from MARINOL or from the underlying maternal condition.

8.4 Pediatric Use

The safety and effectiveness of MARINOL have not been established in pediatric patients. Pediatric patients may be more sensitive to neurological and psychoactive effects of MARINOL [see Warnings and Precautions (5.1)].

8.5 Geriatric Use

Clinical studies of MARINOL in AIDS and cancer patients did not include the sufficient numbers of subjects aged 65 and over to determine whether they respond differently from younger subjects.

Elderly patients may be more sensitive to the neuropsychiatric and postural hypotensive effects of MARINOL [see Warnings and Precautions (5.1, 5.2)]. Elderly patients with dementia are at increased risk for falls as a result of their underlying disease state, which may be exacerbated by the CNS effects of somnolence and dizziness associated with MARINOL [see Warnings and Precautions (5.1)]. These patients should be monitored closely and placed on fall precautions prior to initiating MARINOL therapy. In antiemetic studies, no difference in efficacy was apparent in patients greater than 55 years of age compared to younger patients.

In general, dose selection for an elderly patient should be cautious, usually starting at the low end of the dosing range, reflecting the greater frequency of falls, decreased hepatic, renal, or cardiac function, increased sensitivity to psychoactive effects, and of concomitant disease or other drug therapy [see Dosage and Administration (2.1, 2.2)].

8.6 Effect of CYP2C9 Polymorphism

Published data suggest that systemic clearance of dronabinol may be reduced and concentrations may be increased in the presence of CYP2C9 genetic polymorphism. Monitoring for potentially increased adverse reactions is recommended in patients known to carry genetic variants associated with diminished CYP2C9 function [see Clinical Pharmacology (12.5)].

9 DRUG ABUSE AND DEPENDENCE

9.1 Controlled Substance

MARINOL contains dronabinol capsules, a Schedule III controlled substance.

9.2 Abuse

MARINOL contains dronabinol, the main psychoactive component in marijuana. Ingestion of high doses of dronabinol increases the risk of psychiatric adverse reactions if abused or misused, while continued administration can lead to addiction. Psychiatric adverse reactions may include psychosis, hallucinations, depersonalization, mood alteration, and paranoia.

In an open-label study in patients with AIDS who received MARINOL for up to five months, no abuse, diversion or systematic change in personality or social functioning were observed despite the inclusion of a substantial number of patients with a past history of drug abuse.

Patients should be instructed to keep MARINOL in a secure place out of reach of others for whom the medication has not been prescribed.

9.3 Dependence

Physical dependence is a state that develops as a result of physiological adaptation in response to repeated drug use. Physical dependence manifests by drug class-specific withdrawal symptoms after abrupt discontinuation or a significant dose reduction of a drug. The appearance of a withdrawal syndrome when administration of the drug is terminated is the only actual evidence of physical dependence. Physical dependence can develop during chronic therapy with MARINOL, and develops after chronic abuse of marijuana.

A withdrawal syndrome was reported after the abrupt discontinuation of dronabinol in subjects receiving dosages of 210 mg per day for 12 to 16 consecutive days. Within 12 hours after discontinuation, subjects manifested symptoms such as irritability, insomnia, and restlessness. By approximately 24 hours post-dronabinol discontinuation, withdrawal symptoms intensified to include “hot flashes,” sweating, rhinorrhea, loose stools, hiccoughs, and anorexia. These withdrawal symptoms gradually dissipated over the next 48 hours.

Electroencephalographic changes consistent with the effects of drug withdrawal (hyperexcitation) were recorded in patients after abrupt dechallenge. Patients also complained of disturbed sleep for several weeks after discontinuing therapy with high dosages of dronabinol.

10 OVERDOSAGE

Signs and symptoms of dronabinol overdosage include drowsiness, euphoria, heightened sensory awareness, altered time perception, reddened conjunctiva, dry mouth, tachycardia, memory impairment, depersonalization, mood alteration, urinary retention, reduced bowel motility, decreased motor coordination, lethargy, slurred speech, and postural hypotension. Patients may also experience panic reactions if they have a prior history of nervousness or anxiety, and seizures may occur in patients with existing seizure disorders.

It is not known if dronabinol can be removed by dialysis in cases of overdose.

If over-exposure of MARINOL occurs, call your Poison Control Center at 1-800-222-1222 for current information on the management of poisoning or overdosage.

11 DESCRIPTION

Dronabinol is a cannabinoid designated chemically as (6aR,10aR)-6a,7,8,10a-Tetrahydro-6,6,9- trimethyl-3-pentyl-6H-dibenzo[b,d]-pyran-1-ol. Dronabinol has the following empirical and structural formulas:

C21H30O2 (molecular weight = 314.46)

Dronabinol, the active ingredient in MARINOL (dronabinol capsules, USP), is synthetic delta-9- tetrahydrocannabinol (delta-9-THC).

Dronabinol is a light yellow resinous oil that is sticky at room temperature and hardens upon refrigeration. Dronabinol is insoluble in water and is formulated in sesame oil. It has a pKa of 10.6 and an octanol-water partition coefficient: 6,000:1 at pH 7.

Each MARINOL capsule strength is formulated with the following inactive ingredients: 2.5 mg capsule contains gelatin, glycerin, sesame oil, and titanium dioxide; 5 mg capsule contains iron oxide red and iron oxide black, gelatin, glycerin, sesame oil, and titanium dioxide; 10 mg capsule contains iron oxide red and iron oxide yellow, gelatin, glycerin, sesame oil, and titanium dioxide.

12 CLINICAL PHARMACOLOGY

12.1 Mechanism of Action

Dronabinol is an orally active cannabinoid which has complex effects on the CNS, including central sympathomimetic activity. Cannabinoid receptors have been discovered in neural tissues. These receptors may play a role in mediating the effects of dronabinol.

12.2 Pharmacodynamics

Effects on the Cardiovascular System

Dronabinol-induced sympathomimetic activity may result in tachycardia and/or conjunctival injection. Its effects on blood pressure are inconsistent, but subjects have experienced orthostatic hypotension and/or syncope upon abrupt standing [see Warnings and Precautions (5.2)].

Effects on the Central Nervous System

Dronabinol also demonstrates reversible effects on appetite, mood, cognition, memory, and perception. These phenomena appear to be dose-related, increasing in frequency with higher dosages, and subject to great inter-patient variability. After oral administration, dronabinol has an onset of action of approximately 0.5 to 1 hours and peak effect at 2 to 4 hours. Duration of action for psychoactive effects is 4 to 6 hours, but the appetite stimulant effect of dronabinol may continue for 24 hours or longer after administration.

Tachyphylaxis and tolerance develop to some of the pharmacologic effects of dronabinol with chronic use, suggesting an indirect effect on sympathetic neurons. In a study of the pharmacodynamics of chronic dronabinol exposure, healthy male subjects (N = 12) received 210 mg per day of MARINOL, administered orally in divided doses, for 16 days. An initial tachycardia induced by dronabinol was replaced successively by normal sinus rhythm and then bradycardia. A decrease in supine blood pressure, made worse by standing, was also observed initially. These subjects developed tolerance to the cardiovascular and subjective adverse CNS effects of dronabinol within 12 days of treatment initiation.

Tachyphylaxis and tolerance do not appear to develop to the appetite stimulant effect of MARINOL. In clinical studies involving AIDS patients, the appetite stimulant effect of MARINOL was sustained for up to five months at dosages ranging from 2.5 mg to 20 mg per day.

12.3 Pharmacokinetics

Absorption

Dronabinol (delta-9-THC) is almost completely absorbed (90 to 95%) after single oral doses. Due to the combined effects of first pass hepatic metabolism and high lipid solubility, only 10 to 20% of the administered dose reaches the systemic circulation. Concentrations of both parent drug and its major active metabolite (11-hydroxy-delta-9-THC) peak at approximately 0.5 to 4 hours after oral dosing and decline over several days.

The pharmacokinetics of dronabinol after single doses (2.5, 5, and 10 mg) and multiple doses (2.5, 5, and 10 mg given twice a day) have been studied in healthy subjects.

Summary of Multiple-Dose Pharmacokinetic Parameters of Dronabinol in Healthy Subjects (n=34; 20-45 years) under Fasted Conditions

Mean (SD) PK Parameter Values
Twice Daily Dose | Cmax ng/mL | Median Tmax (range), hr | AUC(0-12) ng•hr/mL
2.5 mg | 1.32 (0.62) | 1.00 (0.50-4.00) | 2.88 (1.57)
5 mg | 2.96 (1.81) | 2.50 (0.50-4.00) | 6.16 (1.85)
10 mg | 7.88 (4.54) | 1.50 (0.50-3.50) | 15.2 (5.52)
Cmax: maximum observed plasma concentration; Tmax: time to maximum observed plasma concentration; AUC(0-12): area under the plasma concentration-time curve from 0 to 12 hours.

A slight increase in dose proportionality on mean Cmax and AUC(0-12) of dronabinol was observed with increasing dose over the dose range studied.

Effect of Food: In a published study, the effect of food on the pharmacokinetics of dronabinol was studied by concomitant dosing of MARINOL® (dronabinol capsules, USP) with a high-fat (59 grams of fat, approximately 50% of total caloric content of the meal), high calorie meal (approximately 950 calories). An appreciable food effect was observed, resulting in a 4-hour delay in mean Tmax and 2.9-fold increase in total exposure (AUCinf), but Cmax was not significantly changed [see Dosage and Administration (2.2)].

Distribution

Dronabinol has an apparent volume of distribution of approximately 10 L/kg, because of its lipid solubility. The plasma protein binding of dronabinol and its metabolites is approximately 97% [see Drug Interactions (7.4)].

Elimination

The pharmacokinetics of dronabinol can be described using a two compartment model with an initial (alpha) half-life of about 4 hours and a terminal (beta) half-life of 25 to 36 hours. Values for clearance average about 0.2 L/kg-hr, but are highly variable due to the complexity of cannabinoid distribution.

Metabolism

Dronabinol undergoes extensive first-pass hepatic metabolism, primarily by hydroxylation, yielding both active and inactive metabolites. Dronabinol and its principal active metabolite, 11-hydroxy-delta-9-THC, are present in approximately equal concentrations in plasma. Published in vitro data indicates that CYP2C9 and CYP3A4 are the primary enzymes in the metabolism of dronabinol. CYP2C9 appears to be the enzyme responsible for the formation of the primary active metabolite [see Clinical Pharmacology (12.5)].

Excretion

Dronabinol and its biotransformation products are excreted in both feces and urine. Biliary excretion is the major route of elimination with about half of a radio-labeled oral dose being recovered from the feces within 72 hours as contrasted with 10 to 15% recovered from urine. Less than 5% of an oral dose is recovered unchanged in the feces.

Due to its re-distribution, dronabinol and its metabolites may be excreted at low levels for prolonged periods of time. Following single dose administration, low levels of dronabinol metabolites have been detected for more than 5 weeks in the urine and feces.

In a study of MARINOL involving AIDS patients, urinary cannabinoid/creatinine concentration ratios were studied bi-weekly over a six week period. The urinary cannabinoid/creatinine ratio was closely correlated with dose. No increase in the cannabinoid/creatinine ratio was observed after the first two weeks of treatment, indicating that steady-state cannabinoid levels had been reached. This conclusion is consistent with predictions based on the observed terminal half-life of dronabinol.

Drug Interaction Studies

Formal drug-drug interaction studies have not been conducted with dronabinol.

The enzyme inhibition and induction potential of dronabinol and its active metabolite are not completely understood.

Published data showed an increase in the elimination half-life of pentobarbital by 4 hours when concomitantly dosed with dronabinol [see Warnings and Precautions (5.1)].

12.5 Pharmacogenomics

Published data indicate a potentially 2-to 3-fold higher dronabinol exposure in individuals carrying genetic variants associated with diminished CYP2C9 function.

13 NONCLINICAL TOXICOLOGY

13.1 Carcinogenesis, Mutagenesis, Impairment of Fertility

In 2-year carcinogenicity studies, there was no evidence of carcinogenicity in rats at doses up to 50 mg/kg/day dronabinol (approximately 20 times the MRHD in AIDS patients on a body surface area basis) or in mice at doses up to 500 mg/kg/day (approximately 100 times the MRHD in AIDS patients on a body surface area basis).

Dronabinol was not genotoxic in the Ames tests, the in vitro chromosomal aberration test in Chinese hamster ovary cells, and the in vivo mouse micronucleus test. However, dronabinol produced a weak positive response in a sister chromatid exchange test in Chinese hamster ovary cells.

In a long-term study (77 days) in rats, oral administration of dronabinol at doses of 30 to 150 mg/m^2, equivalent to 2 to 10 times the MRHD of 15 mg/m^2/day in AIDS patients or 0.3 to 1.5 times the MRHD of 90 mg/m^2/day in cancer patients, reduced ventral prostate, seminal vesicle and epididymal weights and caused a decrease in seminal fluid volume. Decreases in spermatogenesis, number of developing germ cells, and number of Leydig cells in the testis were also observed. However, sperm count, mating success, and testosterone levels were not affected. The significance of these animal findings in humans is not known.

14 CLINICAL STUDIES

The effectiveness of MARINOL has been established based on studies for the treatment of anorexia associated with weight loss in patients with AIDS and nausea and vomiting associated with cancer chemotherapy in patients who have failed to respond adequately to conventional antiemetic treatments.

14.1 Appetite Stimulation

The appetite stimulant effect of MARINOL in the treatment of AIDS-related anorexia associated with weight loss was studied in a randomized, double-blind, placebo-controlled study involving 139 patients. The initial dosage of MARINOL in all patients was 5 mg/day, administered in doses of 2.5 mg one hour before lunch and one hour before dinner. In pilot studies, early morning administration of MARINOL appeared to have been associated with an increased frequency of adverse experiences, as compared to dosing later in the day. The effect of MARINOL on appetite, weight, mood, and nausea was measured at scheduled intervals during the six-week treatment period. Side effects (feeling high, dizziness, confusion, somnolence) occurred in 13 of 72 patients (18%) at this dosage level and the dosage was reduced to 2.5 mg/day, administered as a single dose at supper or bedtime.

Of the 112 patients that completed at least 2 visits in the randomized, double-blind, placebo-controlled study, 99 patients had appetite data at 4-weeks (50 received MARINOL and 49 received placebo) and 91 patients had appetite data at 6-weeks (46 received MARINOL and 45 received placebo). A statistically significant difference between MARINOL and placebo was seen in appetite as measured by the visual analog scale at weeks 4 and 6 (see figure). Trends toward improved body weight and mood, and decreases in nausea were also seen.

After completing the 6-week study, patients were allowed to continue treatment with MARINOL in an open-label study, in which there was a sustained improvement in appetite.

16 HOW SUPPLIED/STORAGE AND HANDLING

MARINOL® (dronabinol capsules, USP)

2.5 mg white capsules (Identified M2).

NDC 53097-571-60 (Bottle of 60 capsules).

5 mg dark brown capsules (Identified M5).

NDC 53097-572-60 (Bottle of 60 capsules).

10 mg orange capsules (Identified MX).

NDC 53097-573-60 (Bottle of 60 capsules).

Storage Conditions

MARINOL capsules should be packaged in a well-closed container and stored in a cool environment between 8° and 15°C (46° and 59°F) and alternatively could be stored in a refrigerator.

Protect from freezing.

17 PATIENT COUNSELING INFORMATION

Advise the patient to read the FDA-approved patient labeling (Patient Information).

Neuropsychiatric Adverse Reactions [see Warnings and Precautions (5.1)]

- Advise patients that psychiatric adverse reactions may occur, especially in patients with a past psychiatric history or in those receiving other drugs also associated with psychiatric effects, and to report to their healthcare provider any new or worsening psychiatric symptoms.
- Advise patients, especially elderly patients, that cognitive impairment or an altered mental state may also occur during treatment with MARINOL and to report to their healthcare provider if they develop signs or symptoms of cognitive impairment.
- Advise patients not to operate motor vehicles or other dangerous machinery until they are reasonably certain that MARINOL does not affect them adversely. Alert patients to the potential for additive central nervous system depression if MARINOL is used concomitantly with alcohol or other CNS depressants such as benzodiazepines and barbiturates.

Hemodynamic Instability

Advise patients, especially those with cardiac disorders, to report to their healthcare provider if they experience any signs or symptoms of hemodynamic instability, including hypotension, hypertension, syncope or tachycardia, especially after initiating or increasing the dosage of MARINOL [see Warnings and Precautions (5.2)].

Seizures Advise patients to discontinue MARINOL and contact a healthcare provider immediately if they experience a seizure [see Warnings and Precautions (5.3)].

Multiple Substance Abuse

Inform patients with a history of substance abuse or dependence, including marijuana or alcohol, that they may be more likely to abuse MARINOL. Advise patients to report to their healthcare provider if they develop abuse behaviors or conditions [see Warnings and Precautions (5.4)].

Paradoxical Nausea, Vomiting, or Abdominal Pain

Advise patients to report worsening nausea, vomiting or abdominal pain to their healthcare provider [see Warnings and Precautions (5.5)]. Pregnancy

Advise pregnant women of the potential risk to a fetus and to avoid use of MARINOL during pregnancy [see Use in Specific Populations (8.1)].

Lactation

- Advise HIV infected women with anorexia associated with weight loss, not to breastfeed because HIV can be passed to the baby through the breast milk.
- Advise women with nausea and vomiting associated with cancer chemotherapy that breastfeeding infants should have their weight monitored [see Use in Specific Populations (8.2)].

Manufactured by: Patheon Softgels Inc.

High Point, NC 27265

Manufactured for: Alkem Laboratories Ltd.,

Mumbai - 400 013, INDIA.

Distributed by: ThePharmaNetwork

Parsippany, New Jersey 07054

1248F00 01/23

PATIENT INFORMATION

MARINOL® (mare in all) (dronabinol) capsules, for oral use, CIII

What is the most important information I should know about MARINOL?

MARINOL can cause serious side effects, including:

- Worsening mental (psychiatric) symptoms. Psychiatric symptoms can worsen in people who have mania, depression, or schizophrenia and who take MARINOL. MARINOL taken with medicines that cause psychiatric symptoms can worsen psychiatric symptoms. Elderly people who take MARINOL may have a greater risk of having psychiatric symptoms. Tell your doctor if you have new or worsening mood symptoms, including symptoms of mania, depression, or schizophrenia.

- Problems thinking clearly. Tell your doctor if you have trouble remembering things, concentrating, have increased sleepiness, or confusion. Elderly people may have a greater risk of having problems thinking clearly.
- Changes in your blood pressure. MARINOL may increase or decrease your blood pressure, especially when you start taking MARINOL or when your dose is changed. Tell your doctor if you have signs or symptoms of changes in your blood pressure including: headaches, vision problems, dizziness, feeling lightheaded, fainting, or a fast heartbeat. Elderly people, especially those with dementia, and people with heart problems may have an increased risk of changes in blood pressure and an increased risk of falls.

What is MARINOL?

- MARINOL is a prescription medicine used in adults to treat:
  - loss of appetite (anorexia) in people with AIDS (Acquired Immune Deficiency Syndrome) who have lost weight.
  - nausea and vomiting caused by anti-cancer medicine (chemotherapy) in people whose nausea and vomiting have not improved with usual anti-nausea medicines.

MARINOL is a controlled substance (CIII) because it contains dronabinol, which can be a target for people who abuse prescription medicines or street drugs. Keep your MARINOL in a safe place to protect it from theft. Never give your MARINOL to anyone else because it may cause death or harm them. Selling or giving away this medicine is against the law.

It is not known if MARINOL is safe and effective in children.

Do not take MARINOL if you:

- had an allergic reaction to dronabinol. Signs and symptoms of an allergic reaction to dronabinol include: swelling of the lips, hives, a rash over your whole body, mouth sores, skin burning, flushing, and throat tightness.
- had an allergic reaction to sesame oil.

Before taking MARINOL, tell your doctor about all of your medical conditions, including if you:

- have or had heart problems.
- have or had problems with drug abuse or dependence.
- have or had problems with alcohol abuse or dependence.
- have or had mental health problems including mania, depression, or schizophrenia.
- have had a seizure or have a medical condition that may increase your risk of having a seizure.
- are pregnant or plan to become pregnant. MARINOL may harm your unborn baby. Avoid the use of MARINOL if you are pregnant.
- are breastfeeding or plan to breastfeed. It is not known if MARINOL passes into your breast milk. Talk to your doctor about the best way to feed your baby if you take MARINOL. The Centers for Disease Control and Prevention recommends that mothers with HIV not breastfeed because they can pass the HIV through their breast milk to the baby. If you are being treated for nausea and vomiting caused by anti-cancer medicine and you breastfeed while taking MARINOL, your doctor should check the weight of your baby regularly.

Tell your doctor about all the medicines you take or have taken in the last 14 days, including prescription and over-the-counter medicines, vitamins, and herbal supplements. MARINOL and certain other medicines can affect each other, causing serious side effects.

How should I take MARINOL?

- Take MARINOL exactly as your doctor tells you to. Your doctor may change your dose after seeing how it affects you. Do not change your dose unless your doctor tells you to change it.
- If you are an adult with AIDS with loss of appetite and weight loss:
  - MARINOL is usually taken 2 times each day, 1 hour before lunch and 1 hour before dinner. If you are elderly or unable to tolerate this dose of MARINOL, your doctor may prescribe MARINOL to be taken 1 time each day, 1 hour before dinner or bedtime to reduce your chance of having nervous system problems.
- If you are an adult with nausea and vomiting caused by anti-cancer medicine:
  - MARINOL is usually taken 1 to 3 hours before your chemotherapy treatment and then every 2 to 4 hours after chemotherapy for up to 4 to 6 doses each day. If you are elderly, your doctor may prescribe MARINOL to be taken 1 to 3 hours before your chemotherapy, 1 time each day to reduce your chance of having nervous system problems.
  - Take your first dose of MARINOL on an empty stomach at least 30 minutes before eating. After your first dose of MARINOL, you can take MARINOL with or without food. Always take your dose at the same time in relation to your meal times for each chemotherapy treatment.
- If you take too much MARINOL, call your Poison Control Center at 1-800-222-1222 right away.

What should I avoid while taking MARINOL?

- Do not drive, operate machinery, or do other dangerous activities until you know how MARINOL affects you. MARINOL taken with other medicines that cause dizziness, confusion, and sleepiness may make these symptoms worse.

What are the possible side effects of MARINOL?

MARINOL may cause serious side effects, including:

- See “What is the most important information I should know about MARINOL?”
- Seizures. MARINOL may increase your risk of seizures. Stop taking MARINOL and call your doctor and get medical care right away if you have a seizure during treatment with MARINOL.
- Drug and alcohol abuse. You may have an increased risk of abusing MARINOL if you have a history of drug or alcohol abuse or dependence, including marijuana. Tell your doctor if you develop abuse behaviors such as increased irritability, nervousness, restlessness or want more or higher doses of MARINOL during your treatment.
- Nausea, vomiting, or stomach-area (abdominal) pain. Tell your doctor if you have nausea, vomiting, or abdominal pain or if your nausea, vomiting, or abdominal pain gets worse during treatment with MARINOL.

The most common side effects of MARINOL include:

- dizziness

- abnormal thoughts

- feeling extremely happy (euphoria)

- stomach-area (abdominal) pain

- overly suspicious or feeling people want to harm you (paranoid reaction)

- nausea

- sleepiness

- vomiting

These are not all the possible side effects of MARINOL. Tell your doctor if you have any side effect that bothers you or does not go away. Call your doctor for medical advice about side effects. You may report side effects to FDA at 1-800-FDA-1088.

How should I store MARINOL?

- Store MARINOL in a cool place such as in a refrigerator, at a temperature between 46°F to 59°F (8°C to 15°C).

- Do not freeze MARINOL capsules.

- Keep the MARINOL container closed tightly.

Keep MARINOL and all medicines out of the reach of children.

General information about the safe and effective use of MARINOL.

Medicines are sometimes prescribed for purposes other than those listed in a Patient Information leaflet. Do not use MARINOL for a condition for which it was not prescribed. Do not give MARINOL to other people, even if they have the same symptoms that you have. It may harm them. You can ask your doctor or pharmacist for information about MARINOL that is written for health professionals.

What are the ingredients in MARINOL?

Active ingredient: dronabinol

Inactive ingredients: 2.5 mg capsules contain gelatin, glycerin, sesame oil, and titanium dioxide; 5 mg capsules contain iron oxide red and iron oxide black, gelatin, glycerin, sesame oil, and titanium dioxide; 10 mg capsules contain iron oxide red and iron oxide yellow, gelatin, glycerin, sesame oil, and titanium dioxide.

Manufactured by: Patheon Softgels Inc. High Point, NC 27265

Manufactured for: Alkem Laboratories Ltd.,

Mumbai - 400 013, INDIA.

Distributed by: ThePharmaNetwork

Parsippany, New Jersey 07054

For more information, go to www.thepharmanetwork.com or call 1-877-272-7901.

This Patient Information has been approved by the U.S. Food and Drug Administration.

Revised: January, 2023

PACKAGE LABEL.PRINCIPAL DISPLAY PANEL

PRINCIPAL DISPLAY PANEL- BOTTLE OF 60 CAPSULES

NDC 53097-571-60

MARINOL®(dronabinol Capsules, USP)

2.5 mg

Rx Only

60 Capsules

ThePharmaNetwork, LLC

PRINCIPAL DISPLAY PANEL- CARTON OF 60 CAPSULES

NDC 53097-571-60

MARINOL(dronabinol Capsules, USP)

2.5 mg

PRESCRIPTION REPACK

UNIT-OF-USE

Rx Only

60 Capsules

ThePharmaNetwork, LLC

PRINCIPAL DISPLAY PANEL- BOTTLE OF 60 CAPSULES

NDC 53097-572-60

MARINOL®(dronabinol Capsules, USP)

5 mg

Rx Only

60 Capsules

ThePharmaNetwork, LLC

PRINCIPAL DISPLAY PANEL- CARTON OF 60 CAPSULES

NDC 53097-572-60

MARINOL(dronabinol Capsules, USP)

5 mg

PRESCRIPTION REPACK

UNIT-OF-USE

Rx Only

60 Capsules

ThePharmaNetwork, LLC

PRINCIPAL DISPLAY PANEL- BOTTLE OF 60 CAPSULES

NDC 53097-573-60

MARINOL®(dronabinol Capsules, USP)

10 mg

Rx Only

60 Capsules

ThePharmaNetwork, LLC

PRINCIPAL DISPLAY PANEL- CARTON OF 60 CAPSULES

NDC 53097-573-60

MARINOL(dronabinol Capsules, USP)

10 mg

PRESCRIPTION REPACK

UNIT-OF-USE

Rx Only

60 Capsules

ThePharmaNetwork, LLC